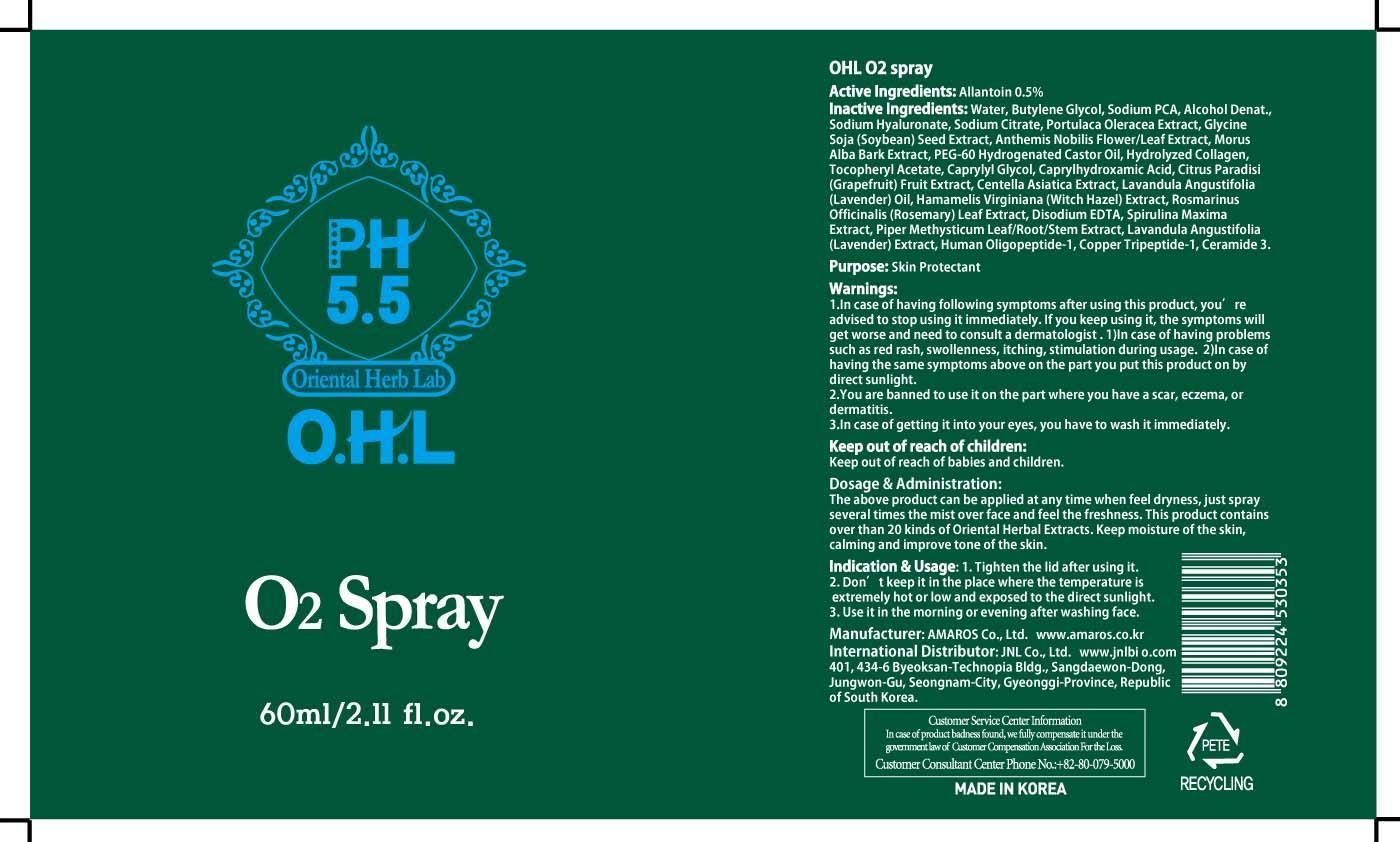 DRUG LABEL: OHL O2
NDC: 60899-040 | Form: SPRAY
Manufacturer: AMAROS CO., LTD.
Category: otc | Type: HUMAN OTC DRUG LABEL
Date: 20190411

ACTIVE INGREDIENTS: Allantoin 0.3 mg/60 mL
INACTIVE INGREDIENTS: Water; Butylene Glycol

ACTIVE INGREDIENT

Active Ingredients: Allantoin 0.5%

INACTIVE INGREDIENT

Inactive Ingredients: Water, Butylene Glycol, Sodium PCA, Alcohol Denat., Sodium Hyaluronate, Sodium Citrate, Portulaca Oleracea Extract, Glycine Soja (Soybean) Seed Extract, Anthemis Nobilis Flower/Leaf Extract, Morus Alba Bark Extract, PEG-60 Hydrogenated Castor Oil, Hydrolyzed Collagen, Tocopheryl Acetate, Caprylyl Glycol, Caprylhydroxamic Acid, Citrus Paradisi (Grapefruit) Fruit Extract, Centella Asiatica Extract, Lavandula Angustifolia (Lavender) Oil, Hamamelis Virginiana (Witch Hazel) Extract, Rosmarinus Officinalis (Rosemary) Leaf Extract, Disodium EDTA, Spirulina Maxima Extract, Piper Methysticum Leaf/Root/Stem Extract, Lavandula Angustifolia (Lavender) Extract, Human Oligopeptide-1, Copper Tripeptide-1, Ceramide 3.

PURPOSE

Purpose: Skin Protectant

WARNINGS

Warnings: 1. In case of having following symptoms after using this product, you're advised to stop using it immediately. If you keep using it, the symptoms will get worse and need to consult a dermatologist. 1) In case of having problems such as red rash, swollenness, itching, stimulation during usage. 2) In case of having the same symptoms above on the part you put this product on by direct sunlight. 2. You are banned to use it on the part where you have a scar, eczema, or dermatitis. 3. In case of getting it into your eyes, you have to wash it immediately.

Keep out of reach of children: Keep out of reach of babies and children.

INDICATIONS AND USAGE

Indication and Usage: 1. Tighten the lid after using it. 2. Don't keep it in the place where the temperature is extremely hot or low and exposed to the direct sunlight. 3. Use it in the morning or evening after washing face.

Dosage and Administration: The above product can be applied at any time when feel dryness, just spray several times the mist over face and feel the freshness. This product contains over than 20 kinds of Oriental Herbal Extracts. Keep moisture of the skin, calming and improve tone of the skin.